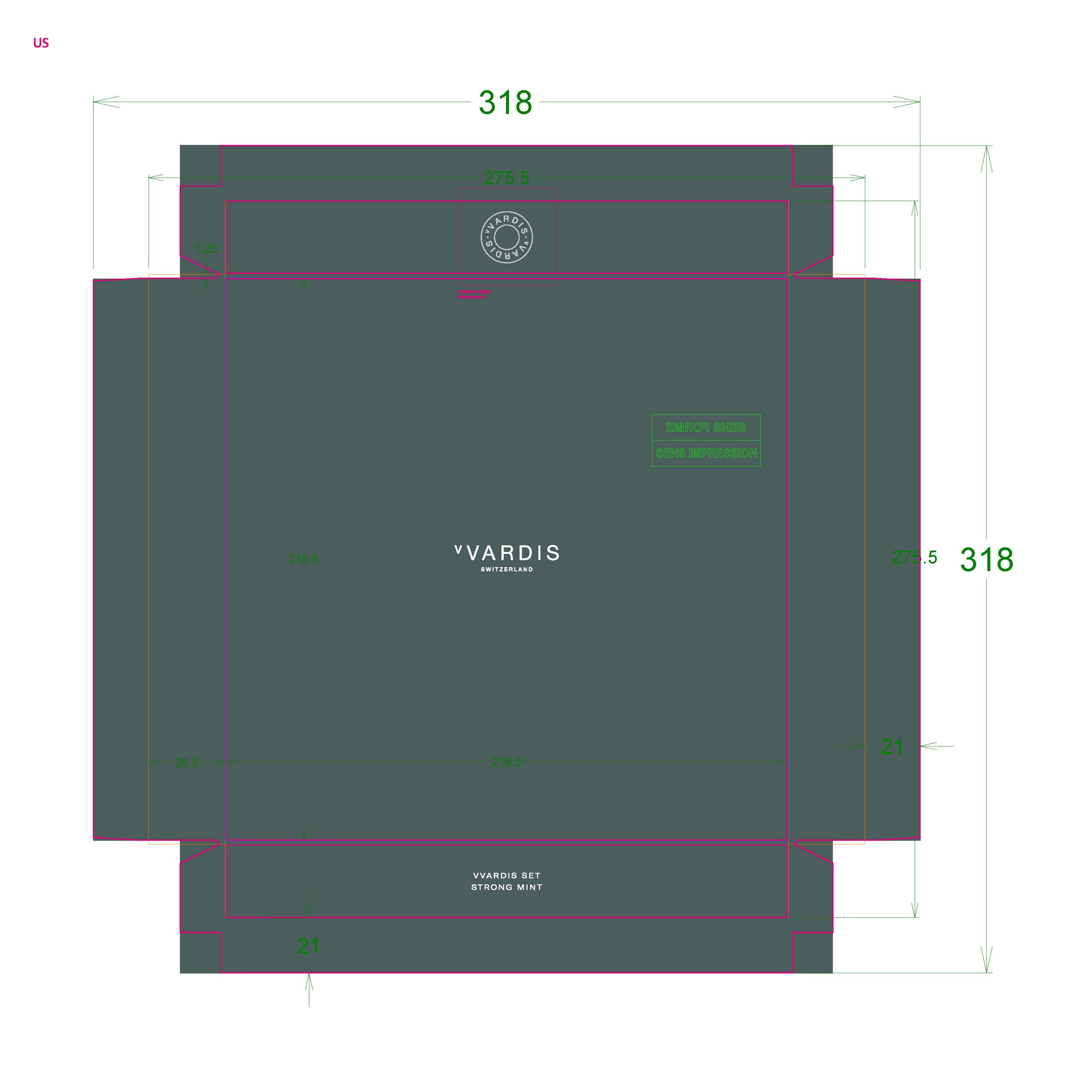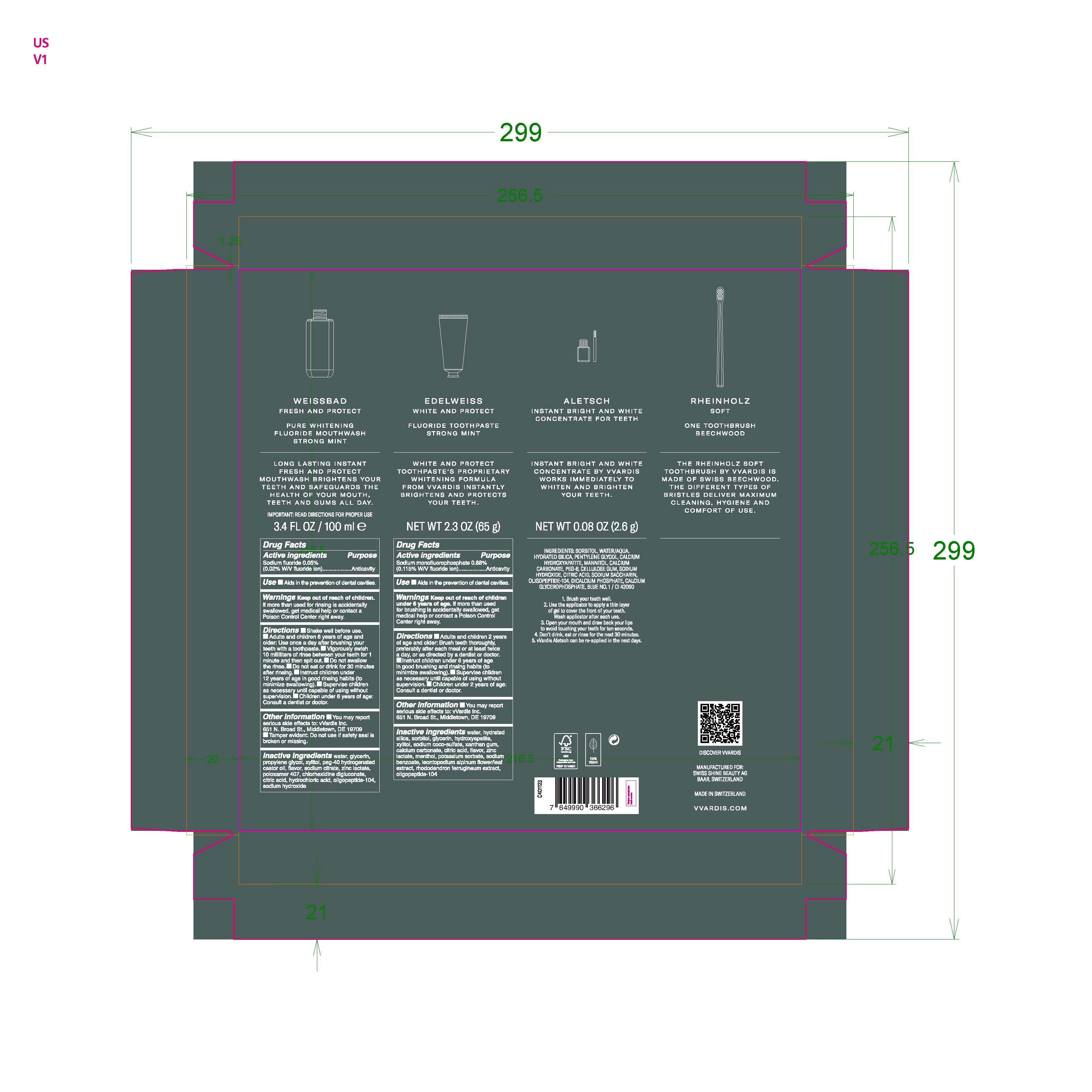 DRUG LABEL: VVARDIS SET STRONG MINT
NDC: 79763-008 | Form: KIT | Route: DENTAL
Manufacturer: Swiss Shine Beauty AG
Category: otc | Type: HUMAN OTC DRUG LABEL
Date: 20210819

ACTIVE INGREDIENTS: SODIUM FLUORIDE 0.05 g/100 mL; SODIUM MONOFLUOROPHOSPHATE 0.88 g/100 g
INACTIVE INGREDIENTS: POLYOXYL 40 HYDROGENATED CASTOR OIL; POLOXAMER 407; XYLITOL; WATER; GLYCERIN; HYDROCHLORIC ACID; CHLORHEXIDINE GLUCONATE; PROPYLENE GLYCOL; CITRIC ACID MONOHYDRATE; SODIUM HYDROXIDE; ZINC LACTATE; SODIUM CITRATE; SODIUM COCO-SULFATE; MENTHOL, UNSPECIFIED FORM; POTASSIUM SORBATE; GLYCERIN; CITRIC ACID MONOHYDRATE; ZINC LACTATE; CALCIUM CARBONATE; RHODODENDRON FERRUGINEUM WHOLE; LEONTOPODIUM ALPINUM FLOWERING TOP; TRIBASIC CALCIUM PHOSPHATE; WATER; HYDRATED SILICA; XANTHAN GUM; SODIUM BENZOATE; SORBITOL; XYLITOL

VVARDIS SET STRONG MINT

ACTIVE INGREDIENT

Mouthwash

Active ingredients

Sodium fluoride 0.05% (0.02% W/V fluoride ion) Purpose Anticavity

ACTIVE INGREDIENT

Toothpaste

Active Ingredients

Sodium monofluorophosphate 0.88% (0.115% W/V flouride ion) Purpose Anticavity

Use

Aids in the prevention of dental cavities.

Keep out of reach of children.

INDICATIONS AND USAGE

Supervise children as necessary until capable of using without supervison.

WARNINGS

Warnings Keep out of reach of children. If more than used for rinsing is accidently swallowed, get medical help or contact a Poison Control Center right away.

WARNINGS

Warnings Keep out of reach of children under 6 years of age. If more than used for brushing is accidentally swallowed, get medical help or contact a Poison Control Center right away.

Directions

Shake well before use.
Adults and children 6 years of age and older: Use once a day after brushing your teeth with a toothpaste.
Vigorously swish 10 milliliters of rinse between your teeth for 1 minute and then spit out.
Do not swallow the rinse.
Do not eat or drink for 30 minutes after rinsing.
Instruct children under 12 years of age in good rinsing habits (to minimize swallowing).
Supervise children as necessary until capable of using without supervision.
Children under 6 years of age: Consult a dentist or doctor.

Directions

Adults and children 2 years of age and older: Brush teeth thoroughly, preferably after each meal or at least twice a day, or as directed by a dentist or doctor.
Instruct children under 6 years of age in good brushing and rinsing habits (to minimize swallowing)
Supervise children as necessary until capable of using without supervison.
Children under 2 years of age: consult a dentist or doctor.

Inactive Ingredients

water, glycerin, propylene glycol, xylitol, peg-40 hydrogenated castor oil, flavor, sodium citrate, zinc lactate, poloxamer 407, chlorhexidine digluconate, citric acid, hydrochloric acid, oligopeptide-104, sodium hydroxide

INACTIVE INGREDIENT

Inactive Ingredients water, hydrated silica, sorbitol, glycerin, hydroxyapatite, xylitol, sodium coco-sulfate, xanthan gum, calcium carbonate, citric acid, flavor, zinc lactate, menthol, potassium sorbate, sodium benzoate, leontopodium alpinum flower/leaf extract, rhododendron ferrugineum extract, oligopeptide-104

PACKAGE LABEL

VVardis Set Strong Mint